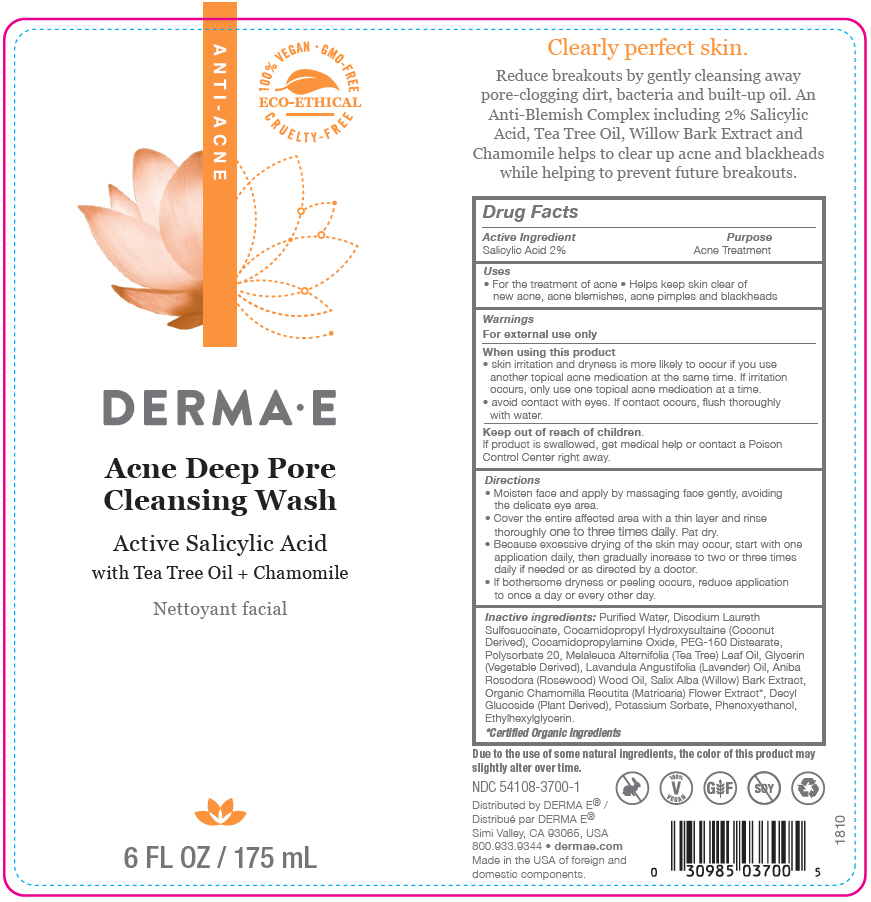 DRUG LABEL: Acne Deep Pore Cleansing Wash
NDC: 54108-3700 | Form: GEL
Manufacturer: derma e
Category: otc | Type: HUMAN OTC DRUG LABEL
Date: 20250115

ACTIVE INGREDIENTS: SALICYLIC ACID 20 mg/1 mL
INACTIVE INGREDIENTS: WATER; DISODIUM LAURETH SULFOSUCCINATE; COCAMIDOPROPYL HYDROXYSULTAINE; COCAMIDOPROPYLAMINE OXIDE; PEG-150 DISTEARATE; POLYSORBATE 20; TEA TREE OIL; GLYCERIN; LAVENDER OIL; ROSEWOOD OIL; SALIX ALBA BARK; MATRICARIA CHAMOMILLA WHOLE; DECYL GLUCOSIDE; POTASSIUM SORBATE; PHENOXYETHANOL; ETHYLHEXYLGLYCERIN

Acne Deep Pore Cleansing Wash

Drug Facts

Active Ingredient

Salicylic Acid 2%

Purpose

Acne Treatment

Uses

- For the treatment of acne
- Helps keep skin clear of new acne, acne blemishes, acne pimples and blackheads

Warnings

For external use only

When using this product

- skin irritation and dryness is more likely to occur if you use another topical acne medication at the same time. If irritation occurs, only use one topical acne medication at a time.
- avoid contact with eyes. If contact occurs, flush thoroughly with water.

Keep out of reach of children.

If product is swallowed, get medical help or contact a Poison Control Center right away.

Directions

- Moisten face and apply by massaging face gently, avoiding the delicate eye area.
- Cover the entire affected area with a thin layer and rinse thoroughly one to three times daily. Pat dry.
- Because excessive drying of the skin may occur, start with one application daily, then gradually increase to two or three times daily if needed or as directed by a doctor.
- If bothersome dryness or peeling occurs, reduce application to once a day or every other day.

Inactive ingredients

Purified Water, Disodium Laureth Sulfosuccinate, Cocamidopropyl Hydroxysultaine (Coconut Derived), Cocamidopropylamine Oxide, PEG-150 Distearate, Polysorbate 20, Melaleuca Alternifolia (Tea Tree) Leaf Oil, Glycerin (Vegetable Derived), Lavandula Angustifolia (Lavender) Oil, Aniba Rosodora (Rosewood) Wood Oil, Salix Alba (Willow) Bark Extract, Organic Chamomilla Recutita (Matricaria) Flower Extract [Certified Organic Ingredients] , Decyl Glucoside (Plant Derived), Potassium Sorbate, Phenoxyethanol, Ethylhexylglycerin.

Distributed by DERMA E®
Simi Valley, CA 93065, USA

PRINCIPAL DISPLAY PANEL - 175 mL Bottle Label

ANTI-ACNE

100% VEGAN • GMO-FREE
ECO-ETHICAL
CRUELTY-FREE

DERMA•E

Acne Deep Pore
Cleansing Wash

Active Salicylic Acid
with Tea Tree Oil + Chamomile

6 FL OZ / 175 mL